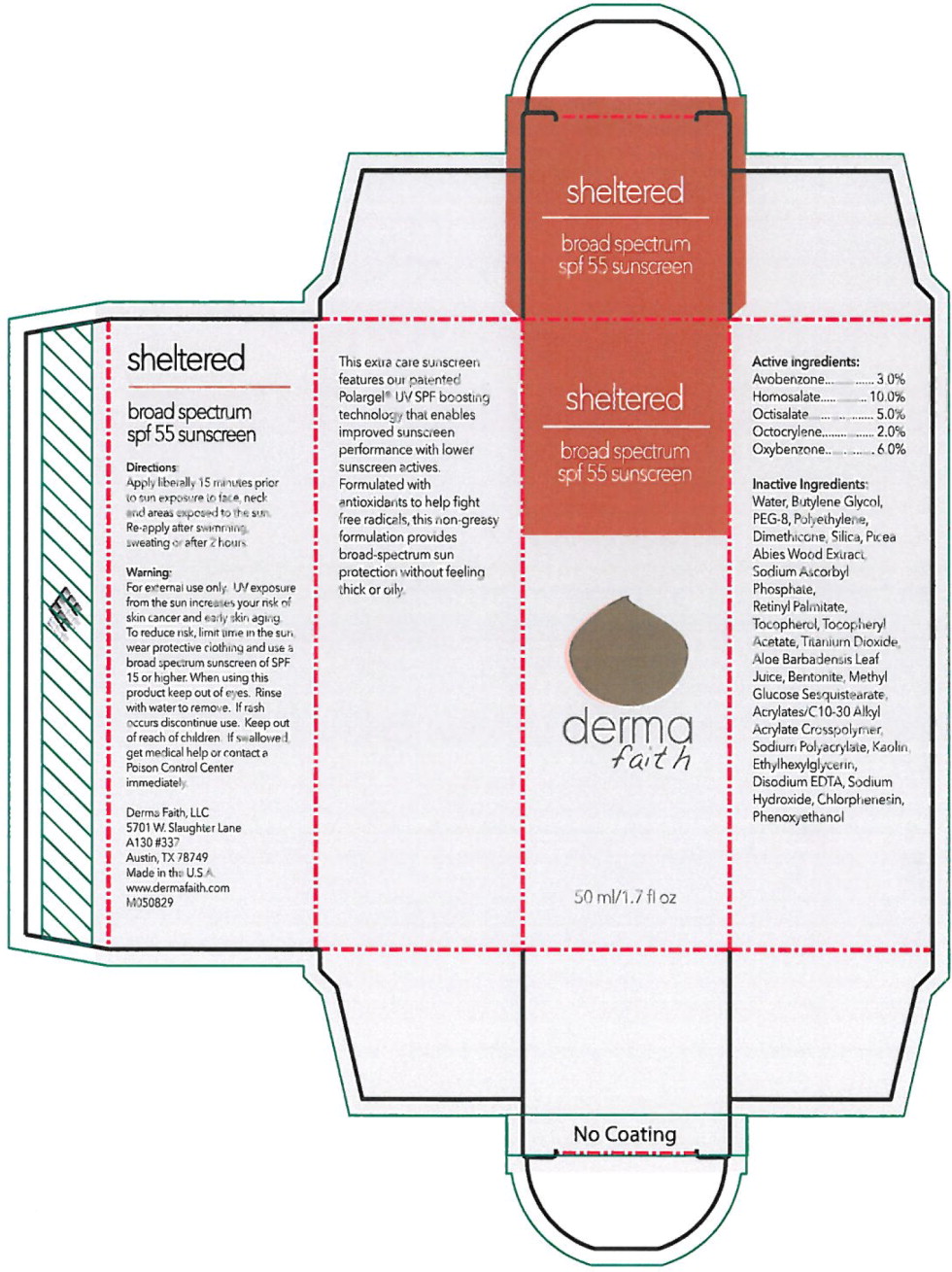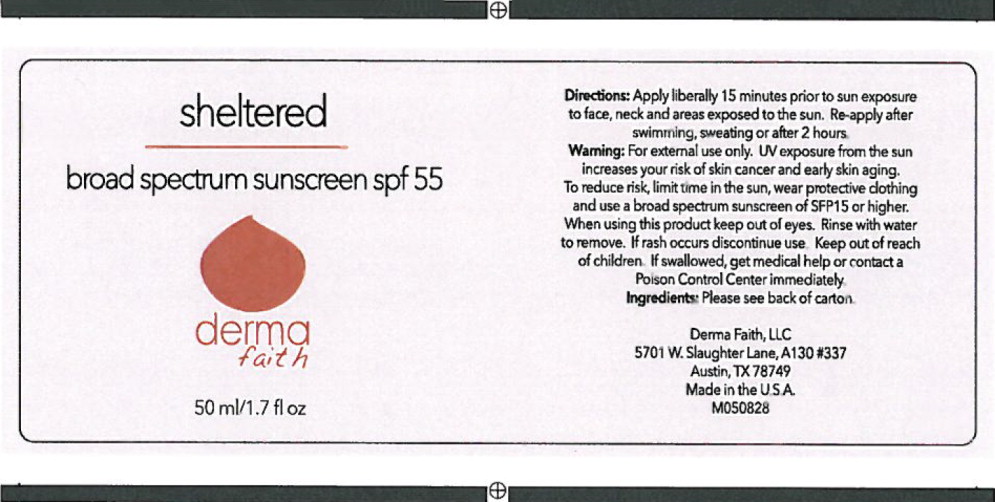 DRUG LABEL: Sheltered Broad Spectrum SPF 55 Sunscreen
NDC: 68634-050 | Form: LIQUID
Manufacturer: AMCOL Health & Beauty Solutions, Inc. DBA
Category: otc | Type: HUMAN OTC DRUG LABEL
Date: 20150831

ACTIVE INGREDIENTS: homosalate 100 g/1 mL; oxybenzone 60 g/1 mL; octisalate 50 g/1 mL; avobenzone 30 g/1 mL; octocrylene 20 g/1 mL
INACTIVE INGREDIENTS: water; butylene glycol; polyethylene glycol 400; high density polyethylene; dimethicone; silicon dioxide; picea abies wood; sodium ascorbyl phosphate; vitamin a palmitate; tocopherol; .alpha.-tocopherol acetate, DL-; titanium dioxide; aloe vera leaf; bentonite; carbomer copolymer type A; sodium polyacrylate (8000 mw); kaolin; ethylhexylglycerin; edetate disodium; sodium hydroxide; chlorphenesin; phenoxyethanol

Sheltered Broad Spectrum Sunscreen SPF 55

HBS Code (Labeler): FP15501-50.1

Distributor: Derma Faith

Human OTC Drug

Active Ingredients:

Avobenzone 3.0%

Homosalate 10.0%

Octisalate 5.0%

Octocrylene 2.0%

Oxybenzone 6.0%

________________________________________________________

PURPOSE

sheltered

broad spectrum

spf 55 sunscreen

derma faith

50 ml/1.7 fl oz

sheltered

broad spectrum

spf 55 sunscreen

Directions:

Apply liberally 15 minutes prior to sun exposure to face, neck and areas exposed to the sun. Re-apply after swimming, sweating or after 2 hours.

Warning:

For external use only. UV exposure from the sun increases your risk of skin cancer and early skin aging. To reduce risk, limit time in the sun, wear protective clothing and use a broad spectrum sunscreen of SPF15 of higher.

When using this product keep out of eyes. Rinse with water to remove. If rash occurs discontinue use.

Keep out of reach of children. If swallowed, get medical help or contact a Poison Control Center immediately.

Derma Faith, LLC
5701 W. Slaughter Lane
A130 #337
Austin, TX 78749
Made in the U.S.A.
www.dermafaith.com
M050829

This extra care sunscreen features our patented Polargel® UV SPF boosting technology that enables improved sunscreen performance with lower sunscreen actives. Formulated with antioxidants to help fight free radicals, this non-greasy formulation provides broad-spectrum sun protection without feeling thick or oily.

Active ingredients:

Avobenzone 3.0%

Homosalate 10.0%

Octisalate 5.0%

Octocrylene 2.0%

Oxybenzone 6.0%

Inactive ingredients:

Water, Butylene Glycol, PEG-8, Polyethylene, Dimethicone, Silica, Picea Abies Wood Extract, Sodium Ascorbyl Phosphate, Retinyl Palmitate, Tocopherol, Tocopheryl Acetate, Titanium Dioxide, Aloe Barbadensis Leaf Juice, Bentonite, Methyl Glucose Sesquistearate, Acrylates/C10-30 Alkyl Acrylate Crosspolymer, Sodium Polyacrylate, Kaolin, Ethylhexylglycerin, Disodium EDTA, Sodium Hydroxide, Chlorphenesin, Phenoxyethanol

________________________________________________________

150831

AMCOL Health & Beauty Solutions, Inc. DBA
301 Laser Lane Lafayette, LA 70507 | www.amcolhpc.com
lauren.haase@amcol.com

Principal Display Panel - Carton Label

sheltered

broad spectrum
spf 55 sunscreen

derma
faith

50 ml/1.7 fl oz.

Principal Display Panel - Bottle Label

sheltered

broad spectrum sunscreen spf 55

derma
faith

50 ml/1.7 fl oz.